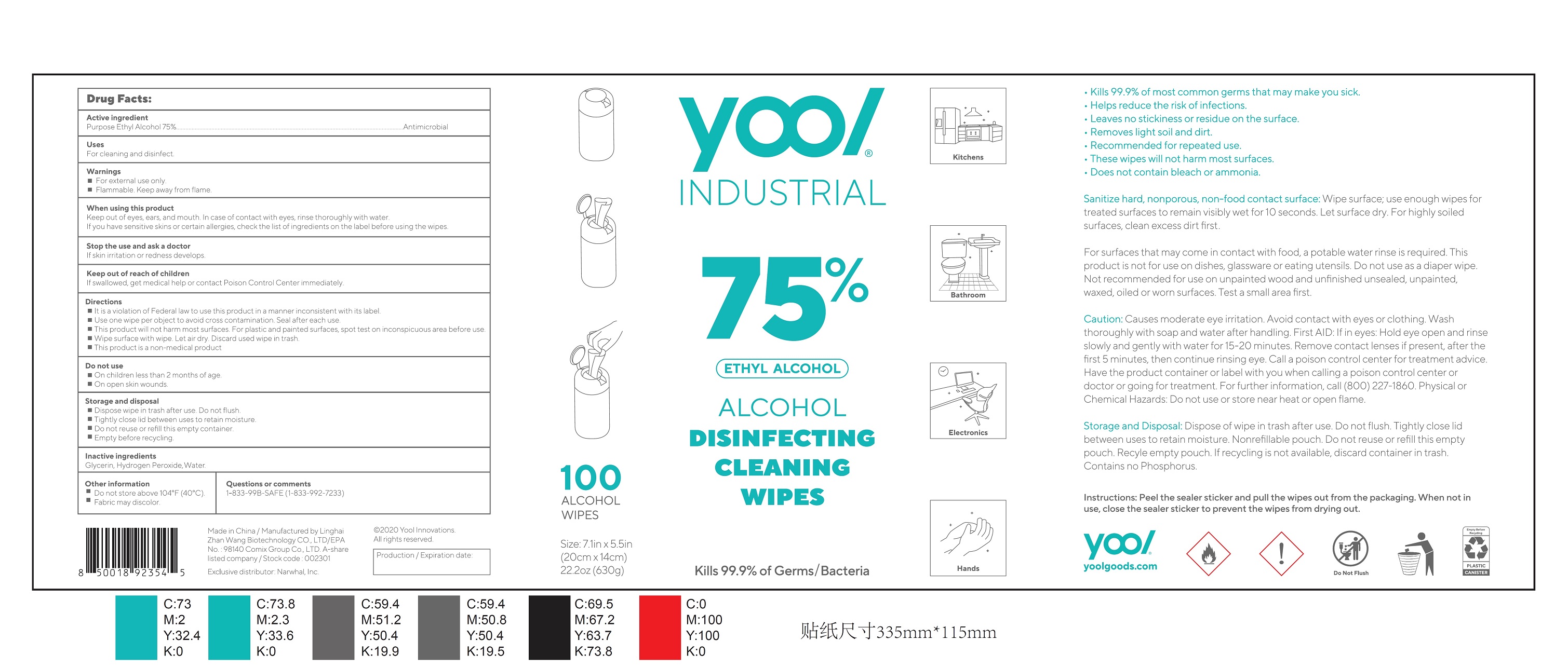 DRUG LABEL: ALCOHOL DISINFECTING CLEANING WIPES
NDC: 75269-004 | Form: CLOTH
Manufacturer: LINGHAI ZHANWANG BIOTECHNOLOGY CO.,LTD.
Category: otc | Type: HUMAN OTC DRUG LABEL
Date: 20231024

ACTIVE INGREDIENTS: ALCOHOL 75 mL/100 mL
INACTIVE INGREDIENTS: WATER; GLYCERIN; HYDROGEN PEROXIDE

75269-004 ALCOHOL DISINFECTING CLEANING WIPES

Active ingredient

Ethyl Alcohol 75%

Purpose

Antimicrobial

Uses

For cleaning and disinfect.

Warnings

For external use only.

Flammable. Keep away from flame.

When using this product

Keep out of eyes, ears, and mouth. In case of contact with eyes, rinse thoroughly with water.

If you have sensitive skins or certain allergies, check the list of ingredients on the label before using the wipes.

Stop the use and ask a doctor

If skin irritation or redness develops.

Keep out of reach of children

If swallowed, get medical help or contact Poison Control Center immediately.

Directions

It is a violation of Federal law to use this product in a manner inconsistent with its label.

Use one wipe per object to avoid cross contamination. Seal after each use.

This product will not harm most surfaces. For plastic and painted surfaces, spot test on inconspicuous area before use.

Wipe surface with wipe. Let air dry. Discard used wipe in trash.

This product is a non-medical product

Do not use

On children less than 2 months of age,

On open skin wounds.

Storage and disposal

Dispose wipe in trash after use. Do not flush.

Tightly close lid between uses to retain moisture.

Do not reuse or refill this empty container.

Empty before recycling.

Inactive ingredients

Glycerin, Hydrogen Peroxide,Water

Other information

Do not store above 104°F (40°C).

Fabric may discolor.

PACKAGE LABEL

100 ALCOHOL WIPES, NDC: 75269-004-01